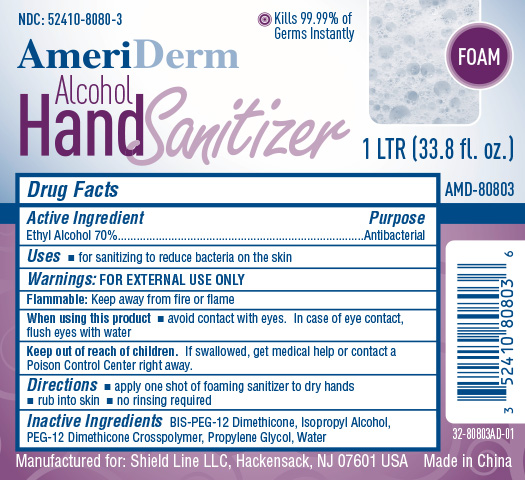 DRUG LABEL: AmeriDerm Foam Alcohol Hand  Sanitizer
NDC: 52410-8080 | Form: LIQUID
Manufacturer: Shield Line LLC
Category: otc | Type: HUMAN OTC DRUG LABEL
Date: 20160608

ACTIVE INGREDIENTS: ALCOHOL 700 mg/1 mL
INACTIVE INGREDIENTS: WATER; BIS-PEG-12 DIMETHICONE (500 MPA.S); ISOPROPYL ALCOHOL; PROPYLENE GLYCOL

DRUG FACTS

Ethyl Alcohol 70%

PURPOSE

Antibacterial

Uses

- for sanitizing to reduce bacteria on skin

WARNINGS

FOR EXTERNAL USE ONLY

Flammable: Keep away from fire or flame

When using this product

- avoid contact with eyes. In case of eye contact, flush eyes with water

KEEP OUT OF REACH OF CHILDREN

If swallowed, get medical help or contact a Poison Control Center right away

Directions

- apply one shot of foaming sanitizer to dry hands
- rub into skin
- no rinsing required

INACTIVE INGREDIENT

BIS-PEG-12 Dimethicone, Isopropyl Alcohol, PEG-12 Dimethicone Crosspolymer, Propylene Glycol, Water